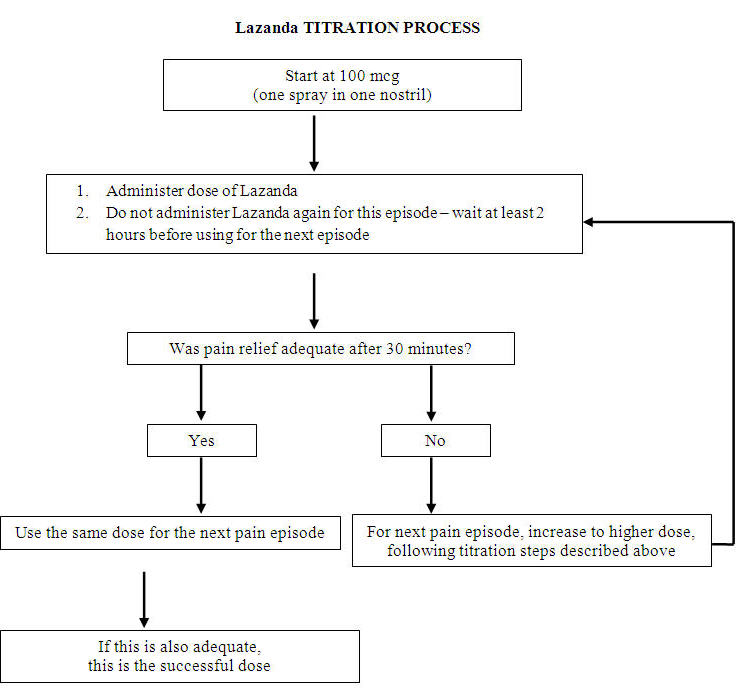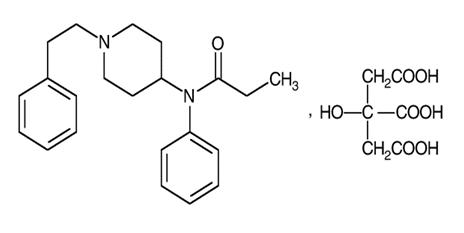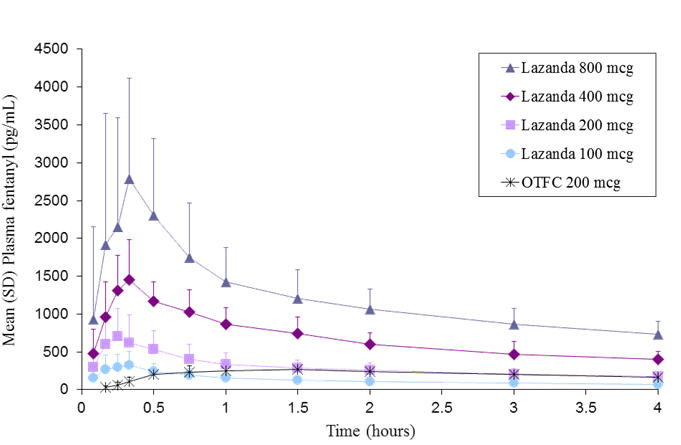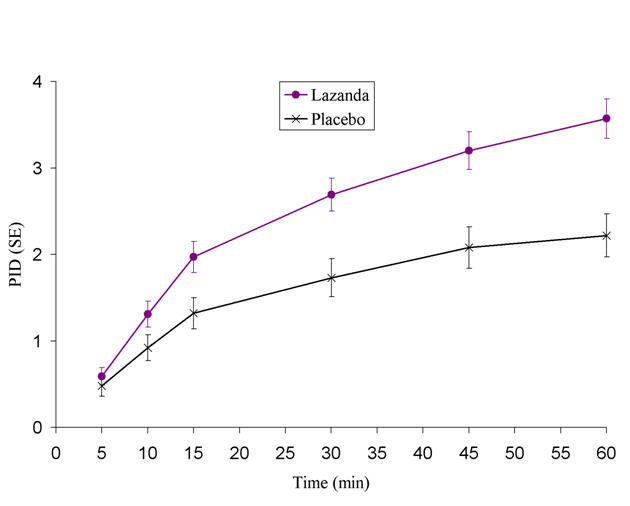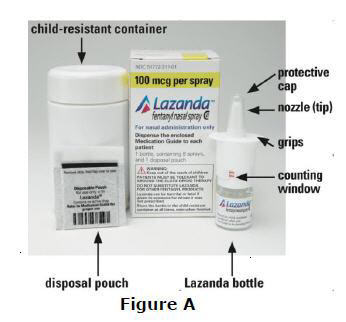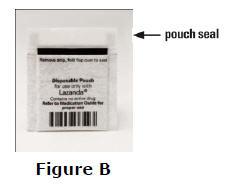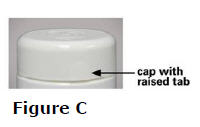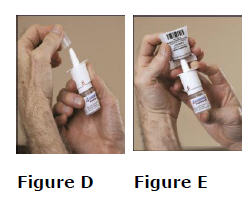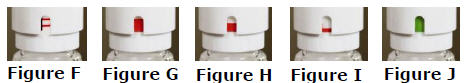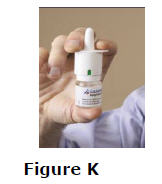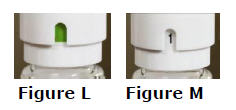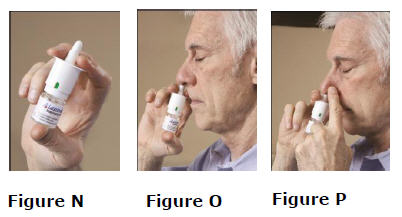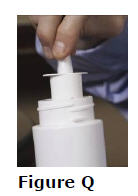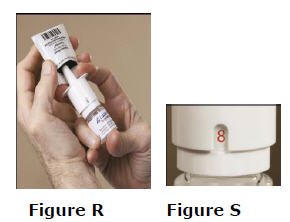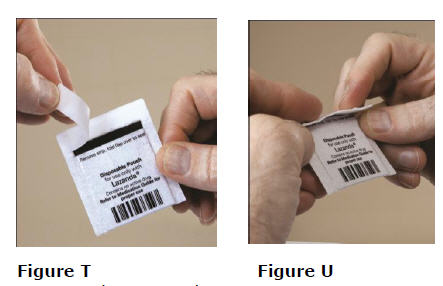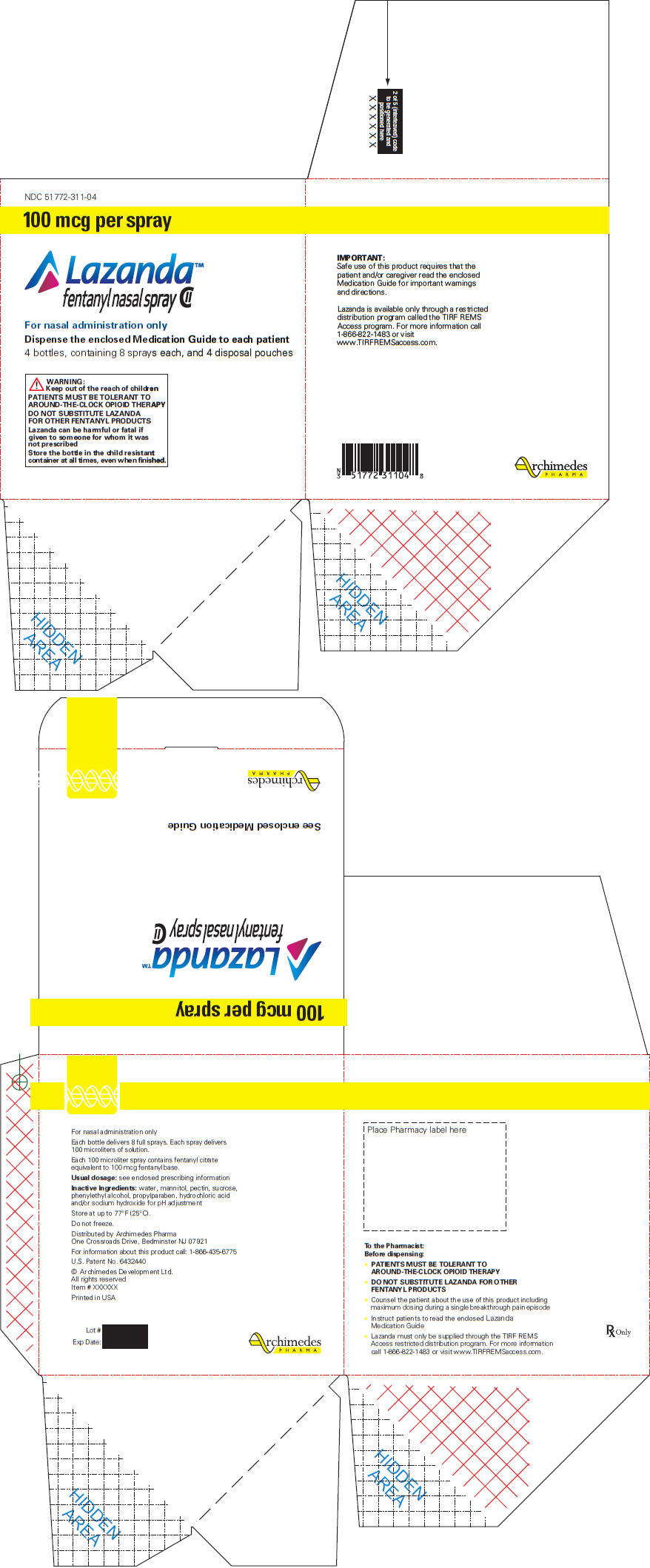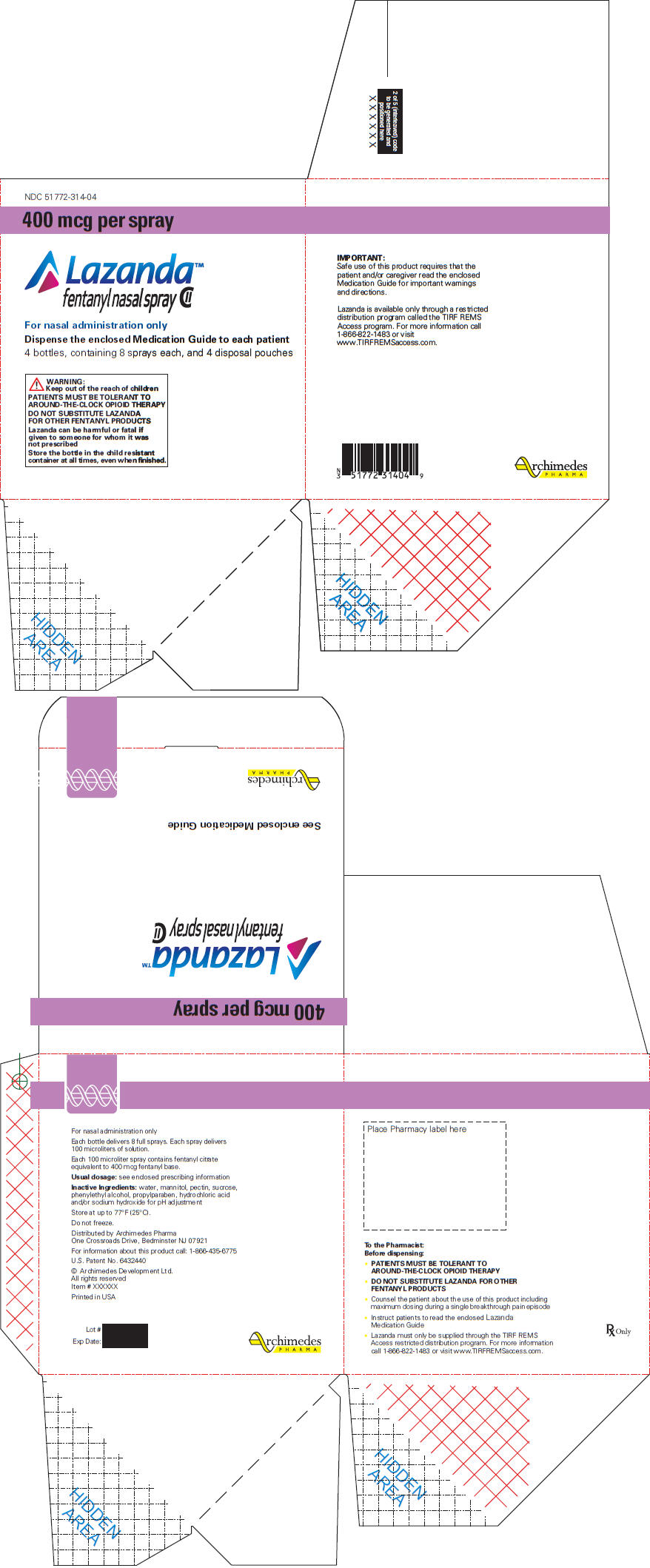 DRUG LABEL: LAZANDA
NDC: 51772-311 | Form: SPRAY
Manufacturer: Archimedes Pharma US Inc.
Category: prescription | Type: HUMAN PRESCRIPTION DRUG LABEL
Date: 20120730
DEA Schedule: CII

ACTIVE INGREDIENTS: Fentanyl Citrate 100 ug/1 1
INACTIVE INGREDIENTS: Water; Mannitol; Pectin; Sucrose; Phenylethyl alcohol; Propylparaben

HIGHLIGHTS OF PRESCRIBING INFORMATION

These highlights do not include all the information needed to use LAZANDA safely and effectively. See full prescribing information for LAZANDA
Lazanda® (Fentanyl) Nasal Spray CII
Initial U.S. Approval: 1968

WARNING: RISK OF RESPIRATORY DEPRESSION, MEDICATION ERRORS, ABUSE POTENTIAL

See full prescribing information for complete boxed warning.

- Due to the risk of fatal respiratory depression, Lazanda is contraindicated in opioid non-tolerant patients (1) and in management of acute or postoperative pain, including headache/migraines. (4)
- Keep out of reach of children. (5.3)
- Use with CYP3A4 inhibitors may cause fatal respiratory depression. (7)
- When prescribing, do not convert patients on a mcg per mcg basis from any other oral transmucosal fentanyl product to Lazanda. (2.1, 5.2)
- When dispensing, do not substitute with any other fentanyl products. (5.2)
- Contains fentanyl, a Schedule II controlled substance with abuse liability similar to other opioid analgesics. (9.1)
- Lazanda is available only through a restricted program called the TIRF REMS Access program. Outpatients, healthcare professionals who prescribe to outpatients, pharmacies, and distributors are required to enroll in the program. (5.10)

RECENT MAJOR CHANGES

Indications and Usage (1) | 12/2011
Warnings and Precautions- TIRF REMS Access Program (5.10) | 12/2011

1 INDICATIONS AND USAGE

Lazanda is an opioid agonist indicated for the management of breakthrough pain in cancer patients 18 years of age and older who are already receiving and who are tolerant to opioid therapy for their underlying persistent cancer pain. [1]

Limitations of Use:

Lazanda may be dispensed only to patients enrolled in the TIRF REMS Access program.

2 DOSAGE AND ADMINISTRATION

- Patients must require and use around-the-clock opioids when taking Lazanda. (1)
- Initial dose of Lazanda for all patients is 100 mcg. [2.1]
- Individually titrate to an effective dose, from 100 mcg to 200 mcg to 400 mcg, and up to a maximum of 800 mcg, that provides adequate analgesia with tolerable side effects. [2.1]
- Dose is a single spray into one nostril or a single spray into each nostril (2 sprays). [2.1]
- Maximum dose is a single spray into one nostril or single spray into each nostril per episode; no more than four doses per 24 hours. [2.1]
- Wait at least 2 hours before treating another episode of breakthrough pain with Lazanda. [2.1]
- During any episode, if adequate pain relief is not achieved within 30 minutes, the patient may use a rescue medication as directed by their healthcare provider.[2]

3 DOSAGE FORMS AND STRENGTHS

- Nasal spray; each spray delivers 100 mcL of solution containing either 100 mcg or 400 mcg fentanyl base. [3] Supplied in a 5 mL bottle containing 8 sprays.

4 CONTRAINDICATIONS

- Opioid–non-tolerant patients. [4]
- Management of acute or postoperative pain including headache/migraine or dental pain. [4]
- Intolerance or hypersensitivity to fentanyl or components of Lazanda. [4]

5 WARNINGS AND PRECAUTIONS

- Clinically significant respiratory and CNS depression can occur. Monitor patients accordingly. [5.1]
- Do not convert patients to Lazanda from other fentanyl products on a mcg per mcg basis, or substitute a Lazanda prescription for another fentanyl product, such substitution may result in fatal overdose. [5.2]
- Lazanda bottles contain medicine that can be fatal to a child. Ensure proper storage and disposal. [5.3, 16.2, 16.3]
- Use with other CNS depressants and potent CYP450 3A4 inhibitors may increase depressant effects including hypoventilation, hypotension, and profound sedation. Consider dosage adjustments if warranted. [5.2, 5.4]
- Titrate Lazanda cautiously in patients with chronic obstructive pulmonary disease or preexisting medical conditions predisposing them to respiratory depression and in patients susceptible to intracranial effects of CO2 retention. [5.2, 5.6, 5.7]

6 ADVERSE REACTIONS

- Most common (frequency ≥5%): vomiting, nausea, dizziness, pyrexia, and constipation. [6.1]

To report SUSPECTED ADVERSE REACTIONS, contact Archimedes Pharma at 1-866-435-6775 or FDA at 1-800-FDA-1088 or www.fda.gov/medwatch.

7 DRUG INTERACTIONS

- See Boxed Warning and Warnings and Precautions (5.4)

8 USE IN SPECIFIC POPULATIONS

- Administer Lazanda with caution to patients with renal or hepatic impairment. [8.6]

FULL PRESCRIBING INFORMATION

WARNING: RISK OF RESPIRATORY DEPRESSION, MEDICATION ERRORS, ABUSE POTENTIAL

RESPIRATORY DEPRESSION

Fatal respiratory depression has occurred in patients treated with immediate-release transmucosal fentanyl, including following use in opioid non-tolerant patients and improper dosing. The substitution of Lazanda for any other fentanyl product may result in fatal overdose.

Due to the risk of respiratory depression, Lazanda is contraindicated in the management of acute or postoperative pain including headache/migraine and in opioid non-tolerant patients. [see Contraindications (4)]

Lazanda must be kept out of reach of children. [see Patient Counseling Information (17.1) and How Supplied/Storage and Handling (16.1)]

The concomitant use of Lazanda with CYP3A4 inhibitors may result in an increase in fentanyl plasma concentrations, and may cause potentially fatal respiratory depression [see Drug Interactions (7)].

MEDICATION ERRORS

Substantial differences exist in the pharmacokinetic profile of Lazanda compared to other fentanyl products that result in clinically important differences in the extent of absorption of fentanyl that could result in fatal overdose.

- When prescribing, do not convert patients on a mcg per mcg basis from any other fentanyl products to Lazanda. (2.1)
- When dispensing, do not substitute a Lazanda prescription for other fentanyl products.

ABUSE POTENTIAL

Lazanda contains fentanyl, an opioid agonist and a Schedule II controlled substance, with an abuse liability similar to other opioid analgesics. Lazanda can be abused in a manner similar to other opioid agonists, legal or illicit. This should be considered when prescribing or dispensing Lazanda in situations where the physician or pharmacist is concerned about an increased risk of misuse, abuse or diversion.

Because of the risk for misuse, abuse, addiction, and overdose, Lazanda is available only through a restricted program required by the Food and Drug Administration, called a Risk Evaluation and Mitigation Strategy (REMS). Under the Transmucosal Immediate Release Fentanyl (TIRF) REMS Access program, outpatients, healthcare professionals who prescribe to outpatients, pharmacies, and distributors must enroll in the program. [see Warnings and Precautions (5.10)] Further information is available at www.TIRFREMSaccess.com or by calling 1-866-822-1483.

1 INDICATIONS AND USAGE

Lazanda (fentanyl) nasal spray is indicated for the management of breakthrough pain in cancer patients 18 years of age and older who are already receiving and who are tolerant to opioid therapy for their underlying persistent cancer pain. Patients considered opioid tolerant are those who are taking at least: 60 mg of oral morphine/day, 25 mcg of transdermal fentanyl/hour, 30 mg oral oxycodone/day, 8 mg oral hydromorphone/day, 25 mg oral oxymorphone/day, or an equianalgesic dose of another opioid for a week or longer. Patients must remain on around-the-clock opioids when taking Lazanda.

Lazanda is contraindicated for patients who are not already tolerant to opioids because life-threatening respiratory depression and death could occur in patients not taking chronic opioids. For this reason, Lazanda is contraindicated in the management of acute or postoperative pain, including headache/migraine, or dental pain. [4]

Lazanda is intended to be prescribed only by healthcare professionals who are knowledgeable of and skilled in the use of Schedule II opioids to treat cancer pain.

Limitations of Use:

As a part of the TIRF REMS Access program, Lazanda may be dispensed only to outpatients enrolled in the program. [see Warnings and Precautions (5.10)]. For inpatient administration of Lazanda (e.g. hospitals, hospices, and long-term care facilities that prescribe for inpatient use), patient enrollment is not required.

2 DOSAGE AND ADMINISTRATION

Healthcare professionals who prescribe Lazanda on an outpatient basis must enroll in the TIRF REMS Access program and comply with the requirements of the REMS to ensure safe use of Lazanda [see Warnings and Precautions (5.10)}.

As with all opioids, the safety of patients using such products is dependent on healthcare professionals prescribing them in strict conformity with their approved labeling with respect to patient selection, dosing, and proper conditions for use.

Open the child-resistant container just prior to product use and always replace the bottle in the child-resistant container between doses.

2.1 Dose Titration

The goal of dose titration is to find the individual patient's effective and tolerable dose. The dose of Lazanda is not predicted from the daily maintenance dose of opioid used to manage the persistent cancer pain and MUST be determined by dose titration.

Starting Dose: Individually titrate Lazanda to a dose that provides adequate analgesia with tolerable side effects. Begin treatment of all patients (including those switching from another fentanyl product) using ONE 100 mcg spray of Lazanda (1 spray in one nostril). Due to differences in pharmacokinetic properties and individual variability, do not switch patients on a mcg per mcg basis from any other fentanyl product to Lazanda as Lazanda is not equivalent with any other fentanyl product, nor is Lazanda a generic version of any other fentanyl product.

If adequate analgesia is obtained within 30 minutes of administration of the 100 mcg single spray, treat subsequent episodes of breakthrough pain with this dose.

Titration steps: If adequate analgesia is not achieved with the first 100 mcg dose, dose escalate in a step-wise manner over consecutive episodes of breakthrough pain until adequate analgesia with tolerable side effects is achieved.

Patients MUST wait at least 2 hours before treating another episode of breakthrough cancer pain with Lazanda.

The titration steps should be:

Lazanda Dose | Using
100 mcg | 1 × 100 mcg spray
200 mcg | 2 × 100 mcg spray (1 in each nostril)
400 mcg | 1 × 400 mcg
800 mcg | 2 × 400 mcg (1 in each nostril)

Patients should confirm the dose of Lazanda that works for them with a second episode of breakthrough pain and review their experience with their physicians to determine if that dose is appropriate, or whether a further adjustment is warranted.

The safety and efficacy of doses higher than 800 mcg have not been evaluated in clinical studies. There are no clinical data to support the use of a combination of dose strengths to treat an episode.

In order to minimize the risk of Lazanda-related adverse reactions and to identify the appropriate dose, it is imperative that patients be supervised closely by health professionals during the titration process.

2.2 Maintenance Treatment

Once an appropriate dose has been established, instruct patients to use that dose for each subsequent breakthrough cancer pain episode. Limit Lazanda use to four or fewer doses per day.

Patients MUST wait at least 2 hours before treating another episode of breakthrough cancer pain with Lazanda.

During any episode of breakthrough cancer pain, if there is inadequate pain relief after 30 minutes following Lazanda dosing or if a separate episode of breakthrough cancer pain occurs before the next dose of Lazanda is permitted (i.e. within 2 hours), the patients may use a rescue medication as directed by their healthcare provider.

2.3 Dose Re-Adjustment

If the response (analgesia or adverse reactions) to the titrated Lazanda dose markedly changes, an adjustment of dose may be necessary to ensure that an appropriate dose is maintained.

If more than four episodes of breakthrough pain are experienced per day, re-evaluate the dose of the long-acting opioid used for persistent underlying cancer pain. If the long-acting opioid or dose of long-acting opioid is changed, re-evaluate and re-titrate the Lazanda dose as necessary to ensure the patient is on an appropriate dose.

Limit the use of Lazanda to treat four or fewer episodes of breakthrough pain per day.

It is imperative that any dose re-titration is monitored carefully by a healthcare professional.

2.4 Administration of Lazanda

Instruct patients on the proper use of Lazanda.

1. Prime the device before use by spraying into the pouch (4 sprays in total) following the instructions for use in the Medication Guide [17.3].
2. Insert the nozzle of the Lazanda bottle a short distance (about ½ inch or 1 cm) into the nose and point towards the bridge of the nose, tilting the bottle slightly.
3. Press down firmly on the finger grips until they hear a "click" and the number in the counting window advances by one.

Advise patients that the fine mist spray is not always felt on the nasal mucosal membrane and to rely on the audible click and the advancement of the dose counter to confirm a spray has been administered.

2.5 Discontinuation of Therapy

For patients no longer requiring opioid therapy, consider discontinuing Lazanda along with a gradual downward titration of other opioids to minimize possible withdrawal effects.

In patients who continue to take their chronic opioid therapy for persistent pain but no longer require treatment for breakthrough pain, Lazanda therapy can usually be discontinued immediately.

3 DOSAGE FORMS AND STRENGTHS

Nasal Spray, Lazanda is formulated to deliver a spray of 100 mcL of solution containing 100 mcg or 400 mcg fentanyl base.

4 CONTRAINDICATIONS

Lazanda is contraindicated in the management of pain in opioid non-tolerant patients, because life-threatening hypoventilation could occur at any dose in patients not already taking around-the-clock opioid therapy.

Patients considered opioid tolerant are those who are taking at least: 60 mg oral morphine/day, 25 mcg transdermal fentanyl/hour, 30 mg oral oxycodone/day, 8 mg oral hydromorphone/day, 25 mg oral oxymorphone/day, or an equianalgesic dose of another opioid for a week or longer.

Lazanda is contraindicated in the management of acute or postoperative pain, including headache/migraine, or dental pain.

Lazanda is contraindicated in patients with known intolerance or hypersensitivity to any of its components or the drug fentanyl. Anaphylaxis and hypersensitivity have been reported in association with the use of other oral transmucosal fentanyl products.

5 WARNINGS AND PRECAUTIONS

5.1 Respiratory Depression

Serious or fatal respiratory depression can occur even at recommended doses in patients using Lazanda. Respiratory depression is more likely to occur in patients with underlying respiratory disorders and elderly or debilitated patients, in opioid non-tolerant patients, or when opioids are given in conjunction with other drugs that depress respiration.

Respiratory depression from opioids is manifested by a reduced urge to breathe and a decreased rate of respiration, often associated with a "sighing" pattern of breathing (deep breaths separated by abnormally long pauses). Carbon dioxide retention from opioid-induced respiratory depression can exacerbate the sedating effects of opioids. This makes overdoses involving drugs with sedative properties and opioids especially dangerous.

5.2 Lazanda and other Fentanyl Products

Lazanda is NOT equivalent to other fentanyl products used to treat breakthrough pain on a mcg per mcg basis. There are differences in the pharmacokinetics of Lazanda relative to other fentanyl products which could potentially result in clinically important differences in the amount of fentanyl absorbed and could result in a fatal overdose.

When prescribing Lazanda to a patient, DO NOT convert from other fentanyl products. Directions for safely converting patients to Lazanda from other fentanyl products are not currently available. (Note: This includes oral, transdermal, or parenteral formulations of fentanyl). Therefore, for opioid-tolerant patients starting treatment for breakthrough pain, the initial dose of Lazanda is 100 mcg. Individually titrate each patient's dose to provide adequate analgesia while minimizing side effects. [See Dosage and Administration (2.1)]

When dispensing Lazanda to a patient, DO NOT substitute it for any other fentanyl product prescription.

5.3 Information for Patients and Their Caregivers

Patients and their caregivers must be instructed that Lazanda contains medicine in an amount that could be fatal to a child.

Patients and their caregivers must be instructed to keep both used and unused bottles in their child-resistant container and out of the reach of children at all times. Partially used bottles represent a special risk to children. As soon as they are no longer required, all used, unopened or partially used bottles must be completely emptied of accessible fentanyl solution by spraying the remaining contents into the carbon-lined pouch. The sealed pouch and the empty bottle should be put into the child-resistant container before discarding in the trash. Hands must be washed with soap and water immediately after handling the pouch. [see Storage and Handling (16.2), Disposal of Lazanda (16.3), and Patient/Caregiver Instructions (17.1)].

Physicians and dispensing pharmacists must question patients and caregivers specifically about the presence of children in the home on a full-time or visiting basis and counsel accordingly regarding the dangers to children of inadvertent exposure to Lazanda.

Lazanda could be fatal to individuals for whom it is not prescribed and for those who are not opioid tolerant.

5.4 Additive CNS Depressant Effects

The concomitant use of Lazanda with other CNS depressants, including other opioids, sedatives or hypnotics, general anesthetics, phenothiazines, tranquilizers, skeletal muscle relaxants, sedating antihistamines, and alcoholic beverages may produce increased depressant effects (e.g., hypoventilation, hypotension, and profound sedation). Concomitant use with potent inhibitors of cytochrome P450 3A4 isoform (e.g., erythromycin, ketoconazole, and certain protease inhibitors) may increase fentanyl levels, resulting in increased depressant effects [see Metabolic Drug Interactions (7.1)].

Patients on concomitant CNS depressants must be monitored for a change in opioid effects and may require adjustment of the dose of Lazanda.

5.5 Effects on Ability to Drive and Use Machines

Opioid analgesics impair the mental and/or physical ability required for the performance of potentially dangerous tasks (e.g., driving a car or operating machinery). Warn patients taking Lazanda of these dangers and counsel them accordingly.

5.6 Chronic Pulmonary Disease

Because potent opioids can cause respiratory depression, cautiously adjust the dose of Lazanda in patients with chronic obstructive pulmonary disease or preexisting medical conditions predisposing them to respiratory depression. In such patients, even normal therapeutic doses of Lazanda may further decrease respiratory drive to the point of respiratory failure.

5.7 Head Injuries and Increased Intracranial Pressure

Administer Lazanda with extreme caution in patients who may be particularly susceptible to the intracranial effects of CO2 retention, such as those with evidence of increased intracranial pressure or impaired consciousness. Opioids may obscure the clinical course of a patient with a head injury; only use opioids if clinically warranted.

5.8 Cardiac Disease

Intravenous fentanyl may produce bradycardia. Use Lazanda with caution in patients with bradyarrhythmias.

5.9 MAO Inhibitors

Lazanda is not recommended for use in patients who have received MAO inhibitors within 14 days, because severe and unpredictable potentiation by MAO inhibitors has been reported with opioid analgesics. [see Non-metabolic Drug Interactions (7.2)].

5.10 Transmucosal Immediate Release Fentanyl (TIRF) Risk Evaluation and Mitigation Strategy (REMS) Access Program

Because of the risk of misuse, abuse, addiction, and overdose [see Drug Abuse and Dependence (9)], Lazanda is available only through a restricted program under a REMS called the TIRF REMS Access program. Under the TIRF REMS Access program, outpatients, healthcare professionals who prescribe to outpatients, pharmacies, and distributors must enroll in the program. For inpatient administration (e.g. hospitals, hospices, and long-term care facilities that prescribe for inpatient use) of Lazanda, patient and prescriber enrollment is not required.

Required components of the TIRF REMS Access program are:

- Healthcare professionals who prescribe Lazanda must review the prescriber educational materials for the TIRF REMS Access program, enroll in the program, and comply with the REMS requirements.
- To receive Lazanda, outpatients must understand the risks and benefits and sign a Patient-Prescriber Agreement.
- Pharmacies that dispense Lazanda must enroll in the program and agree to comply with the REMS requirements.
- Wholesalers and distributers that distribute Lazanda must enroll in the program and distribute only to authorized pharmacies.

Further information, including a list of qualified pharmacies/distributors, is available at www.tirfremsaccess.com or by calling 1-866-822-1483.

6 ADVERSE REACTIONS

6.1 Clinical Studies Experience

Because clinical trials are conducted under widely varying conditions, adverse event rates observed in the clinical trials of a drug product cannot be directly compared to rates in the clinical trials of another drug and may not reflect the rates observed in practice.

The safety of Lazanda has been evaluated in a total of 523 opioid-tolerant patients with breakthrough cancer pain. The average duration of therapy in patients in the long-term study was 73 days, with 153 patients being treated for over 3 months. Patients continuing into the open-label extension period of the safety study have been treated for up to 26 months.

The most commonly observed adverse events seen with Lazanda are typical of opioid side effects, such as nausea, constipation, somnolence, and headache. Expect opioid side effects and manage them accordingly.

The clinical trials of Lazanda were designed to evaluate safety and efficacy in treating breakthrough cancer pain; all patients were also taking concomitant opioids, such as sustained-release morphine, sustained-release oxycodone, or transdermal fentanyl, for their persistent cancer pain. The adverse reaction data presented in Table 1 reflect the actual percentage of patients experiencing each adverse effect among patients who received Lazanda for breakthrough cancer pain along with a concomitant opioid for persistent cancer pain. There has been no attempt to correct for concomitant use of other opioids, duration of Lazanda therapy, or cancer-related symptoms. Adverse events are included regardless of causality or severity. Table 1 lists adverse reactions with an overall frequency of 5% or greater within the total population that occurred during titration by maximum dose received. The ability to assign Lazanda a dose-response relationship to these adverse events is limited by the titration schemes used in these studies.

Table 1: Adverse Reactions That Occurred During Titration at a Frequency of ≥5%
System Organ Class MeDRA preferred term, n (%) | 100 mcg (N=483) | 200 mcg (N=380) | 400 mcg (N=301) | 800 mcg (N=161) | Total (N=516)
Gastrointestinal disorders
Nausea | 19 (4) | 6 (2) | 6 (2) | 5 (3) | 35 (7)
Vomiting | 14 (3) | 10 (3) | 9 (3) | 1 (1) | 33 (6)
Nervous system disorders
Dizziness | 14 (3) | 11 (3) | 6 (2) | 4 (2) | 31 (6)

Table 2 lists, by dose, adverse reactions with an overall frequency of ≥5% within the total population that occurred after a final titrated dose had been determined.

Table 2: Adverse Reactions That Occurred During Maintenance Treatment at a Frequency of ≥5%
System Organ Class MeDRA preferred term, n (%) | 100 mcg (N=61) | 200 mcg (N=68) | 400 mcg (N=109) | 800 mcg (N=108) | Total (N=346)
Gastrointestinal disorders
Vomiting | 8 (13) | 5 (7) | 9 (8) | 12 (11) | 34 (10)
Nausea | 4 (7) | 6 (9) | 4 (4) | 9 (8) | 23 (7)
Constipation | 6 (10) | 1 (1) | 8 (7) | 5 (5) | 20 (6)
General disorders and administration site conditions
Pyrexia | 3 (5) | 5 (7) | 8 (7) | 6 (6) | 22 (6)

The adverse reactions listed below represent those that occurred in ≥1% of patients from clinical trials while receiving Lazanda. Events are classified by system organ class.

Adverse Events (≥1%)
Eye disorders: dry eye, swelling, ptosis, strabismus
Blood and Lymphatic System Disorders: anemia, neutropenia
Cardiac Disorders: cardiorespiratory arrest
Gastrointestinal Disorders: vomiting, nausea, constipation, diarrhea, abdominal pain, gastritis, ascites, dry mouth, dyspepsia, mouth ulcer, proctalgia
General Disorders and Administration Site Conditions: pyrexia, fatigue, edema peripheral, asthenia, edema
Hepatobiliary Disorders: jaundice
Immune System Disorders: hypersensitivity
Infections and Infestations: urinary tract infection, pneumonia, nasopharyngitis, infection, rhinitis, upper respiratory tract infection, bronchitis
Injury, Poisoning and Procedural Complications: fall
Investigations: weight decreased, blood alkaline phosphatase increased
Metabolism and Nutrition Disorders: dehydration, decreased appetite, hyperglycemia, anorexia
Musculoskeletal and Connective Tissue Disorders: back pain, pain in extremity, arthralgia
Nervous System Disorders: dizziness, somnolence, headache, dysgeusia
Psychiatric Disorders: anxiety, insomnia, depression, confusional state, disorientation, agitation
Respiratory, Thoracic and Mediastinal Disorders: dyspnea, epistaxis, cough, pharyngolaryngeal pain, nasal discomfort, rhinorrhea, nasal congestion, postnasal drip, pulmonary embolism
Skin and Subcutaneous Tissue Disorders: pruritus, hyperhidrosis, decubitus ulcer, mouth ulceration
Vascular Disorders: hypertension, deep vein thrombosis

7 DRUG INTERACTIONS

7.1 Metabolic Drug Interactions

Fentanyl is metabolized mainly via the human cytochrome P450 3A4 isoenzyme system (CYP3A4); therefore potential interactions may occur when Lazanda is given concurrently with agents that affect CYP3A4 activity.

CYP3A4 inhibitors

The concomitant use of Lazanda with CYP3A4 inhibitors (e.g., indinavir, nelfinavir, ritonavir, clarithromycin, itraconazole, ketoconazole, nefazodone, saquinavir, telithromycin, aprepitant, diltiazem, erythromycin, fluconazole, grapefruit juice, verapamil, or cimetidine) may result in a potentially dangerous increase in fentanyl plasma concentrations, which could increase or prolong adverse drug effects and may cause potentially fatal respiratory depression. Patients receiving Lazanda who begin therapy with, or increase the dose of, CYP3A4 inhibitors are to be carefully monitored for signs of opioid toxicity over an extended period of time. Increase dose conservatively [see Warnings and Precautions (5.4)].

CYP3A4 inducers

The concomitant use of Lazanda with CYP3A4 inducers (e.g., barbiturates, carbamazepine, efavirenz, glucocorticoids, modafinil, nevirapine, oxcarbazepine, phenobarbital, phenytoin, pioglitazone, rifabutin, rifampin, St. John's wort, or troglitazone) may result in a decrease in fentanyl plasma concentrations, which could decrease the efficacy of Lazanda. Patients receiving Lazanda who stop therapy with, or decrease the dose of, CYP3A4 inducers may experience sudden increase in fentanyl plasma concentrations and are to be monitored for signs of increased Lazanda activity. Adjust the dose of Lazanda accordingly.

7.2 Non-metabolic Drug Interactions

Agents used to treat Allergic Rhinitis

The presence of allergic rhinitis is not expected to affect Lazanda absorption. However, co-administration of a vasoconstrictive nasal decongestant such as oxymetazoline to treat allergic rhinitis leads to lower peak plasma concentrations and a delayed Tmax of fentanyl that may cause Lazanda to be less effective in patients with allergic rhinitis who use such decongestants, thus potentially impairing pain management. Additionally, in view of the possibility that the titration of a patient while they are experiencing an acute episode of rhinitis could lead to incorrect dose identification (particularly if they are using a vasoconstrictive decongestant), titration under these circumstances must be avoided [see Clinical Pharmacology (12.3)].

MAO inhibitor

Concomitant use of Lazanda with an MAO inhibitor, or within 14 days of discontinuing an MAO inhibitor, is not recommended.

8 USE IN SPECIFIC POPULATIONS

8.1 Pregnancy – Category C

There are no adequate and well-controlled studies in pregnant women.

Use Lazanda during pregnancy only if the potential benefit justifies the potential risk to the fetus. No epidemiological studies of congenital anomalies in infants born to women treated with fentanyl during pregnancy have been reported.

Chronic maternal treatment with fentanyl during pregnancy has been associated with transient respiratory depression, behavioral changes, or seizures in newborn infants characteristic of neonatal abstinence syndrome.

In women treated acutely with intravenous or epidural fentanyl during labor, symptoms of neonatal respiratory or neurological depression were no more frequent than would be expected in infants of untreated mothers.

Transient neonatal muscular rigidity has been observed in infants whose mothers were treated with intravenous fentanyl.

Fentanyl is embryocidal in rats as evidenced by increased resorptions in pregnant rats at doses of 30 mcg/kg IV or 160 mcg/kg SC. Conversion to human equivalent doses indicates this is within the range of the human recommended dosing for Lazanda.

Fentanyl citrate was not teratogenic when administered to pregnant animals. Published studies demonstrated that administration of fentanyl (10, 100, or 500 mcg/kg/day) to pregnant rats from day 7 to 21 of their 21 day gestation, via implanted microosmotic minipumps was not teratogenic. The high dose was approximately 3 times the human dose of 800 mcg per pain episode on a mg/m^2 basis. Intravenous administration of fentanyl (10 or 30 mcg/kg) to pregnant female rats from gestation days 6 to 18 was embryo or fetal toxic and caused a slightly increased mean delivery time in the 30 mcg/kg/day group, but it was not teratogenic.

8.2 Labor and Delivery

Fentanyl readily passes across the placenta. Therefore do not use Lazanda during labor and delivery (including caesarean section) since it may cause respiratory depression in the fetus or in the newborn infant.

8.3 Nursing Mothers

Fentanyl is excreted in human milk; therefore, do not use Lazanda in women who are nursing because of the risk of sedation and/or respiratory depression in their infants. Symptoms of opioid withdrawal may occur in infants upon cessation of nursing by women using Lazanda.

8.4 Pediatric Use

The safety and efficacy of Lazanda have not been established in patients below the age of 18 years.

8.5 Geriatric Use

Of the 523 opioid tolerant cancer patients with breakthrough cancer pain in clinical studies of Lazanda, 148 (28%) were aged 60 years and over. No clinically meaningful difference was noted in the safety profile of the group aged over 60 years versus that of younger patients in Lazanda clinical trials.

Elderly patients have been shown to be more sensitive to the effects of fentanyl when administered intravenously compared with the younger population. Therefore, exercise caution when individually titrating Lazanda in elderly patients.

8.6 Patients with Renal or Hepatic Impairment

Insufficient information exists to make recommendations regarding the use of Lazanda in patients with impaired renal or hepatic function. Fentanyl is metabolized primarily via the human CYP3A4 isoenzyme system and the inactive metabolite is mostly eliminated in urine. If the drug is used in these patients, it is to be used with caution because of the hepatic metabolism and renal excretion of fentanyl.

It is recommended that Lazanda be titrated to clinical effect for all patients with special care taken in patients with severe renal or hepatic disease.

8.7 Gender

Both male and female opioid-tolerant cancer patients were studied for the treatment of breakthrough cancer pain. No clinically relevant gender differences were observed in adverse events.

8.8 Patients with Allergic (Seasonal) Rhinitis

The pharmacokinetic and safety profiles of Lazanda in individuals with known allergic (seasonal) rhinitis showed no clinically meaningful differences in rate or extent of exposure to fentanyl, or in local tolerability of Lazanda when compared to Asymptomatic (Unchallenged) state. However, when treated for their rhinitis with oxymetazoline, Lazanda absorption was compromised [see Pharmacokinetics (12.3)].

9 DRUG ABUSE AND DEPENDENCE

9.1 Controlled Substance

Lazanda contains fentanyl, which is a Schedule II controlled substance. Schedule II substances such as fentanyl, hydromorphone, methadone, morphine, oxycodone, and oxymorphone have a high potential for abuse and addiction. Lazanda may be subject to misuse and criminal diversion.

9.2 Abuse and Addiction

Manage the handling of Lazanda to minimize the risk of abuse, including restriction of access and accounting procedures as appropriate to the clinical setting and as required by law [see How Supplied/Storage and Handling (16.1, 16.2)].

Concerns about abuse and addiction should not prevent the proper management of pain. However, all patients treated with opioids require careful monitoring for signs of abuse and addiction, because use of opioid analgesic products carries the risk of addiction even under appropriate medical use.

Addiction is a primary, chronic, neurobiologic disease, with genetic, psychosocial, and environmental factors influencing its development and manifestations. It is characterized by behaviors that include one or more of the following: impaired control over drug use, compulsive use, continued use despite harm, and craving. Drug addiction is a treatable disease, utilizing a multidisciplinary approach, but relapse is common. "Drug-seeking" behavior is very common in addicts and drug abusers.

Abuse and addiction are separate and distinct from physical dependence and tolerance. Be aware that addiction may not be accompanied by concurrent tolerance and symptoms of physical dependence in all addicts. In addition, abuse of opioids can occur in the absence of addiction and is characterized by misuse for nonmedical purposes, often in combination with other psychoactive substances. Since Lazanda may be abused or diverted for nonmedical use, careful record keeping of prescribing information, including quantity, frequency, and renewal requests, is strongly advised.

Proper assessment of patients, proper prescribing practices, periodic reevaluation of therapy, and proper dispensing and storage are appropriate measures that help to limit abuse of opioid drugs.

Contact your State Professional Licensing Board or State Controlled Substances Authority for information on how to prevent and detect abuse or diversion of this product.

9.3 Dependence

Physical dependence is not ordinarily a concern when treating a patient with cancer and chronic pain, and fear of tolerance and physical dependence should not deter using doses that adequately relieve the pain. Guide the administration of Lazanda by the response of the patient.

Opioid analgesics may cause physical dependence. Physical dependence results in withdrawal symptoms in patients who abruptly discontinue the drug. Withdrawal also may be precipitated through the administration of drugs with opioid antagonist activity, e.g., naloxone, nalmefene, or mixed agonist/antagonist analgesics (e.g., pentazocine, butorphanol, buprenorphine, nalbuphine).

Physical dependence usually does not occur to a clinically significant degree until after several weeks of continued opioid usage. Tolerance, in which increasingly larger doses are required in order to produce the same degree of analgesia, initially manifests as a shortened duration of analgesic effect, and subsequently as decreases in the intensity of analgesia.

10 OVERDOSAGE

10.1 Clinical Presentation

The manifestations of overdosage with Lazanda are expected to be similar to those for intravenous fentanyl and other opioids, and are an extension of its pharmacological actions, with the most serious significant adverse effect being hypoventilation [see Clinical Pharmacology (12)].

10.2 Immediate Management

Immediate management of opioid overdose includes removal of the Lazanda pectin gel, if still in the nostril, ensuring a patent airway, physical and verbal stimulation of the patient, and assessment of level of consciousness, ventilatory status, and circulatory status.

10.3 Treatment of Overdosage (Accidental Ingestion) in Opioid Non-Tolerant Patients

Provide ventilatory support, obtain intravenous access, and administer naloxone or other opioid antagonists as clinically indicated. The duration of respiratory depression following overdose may be longer than the effects of the opioid antagonist's action (e.g., the half-life of naloxone ranges from 30 to 81 minutes) and repeated administration may be necessary. Consult the package insert of the individual opioid antagonist for details about such use.

10.4 Treatment of Overdose in Opioid-Tolerant Patients

Provide ventilatory support and obtain intravenous access as clinically indicated. Judicious use of naloxone or another opioid antagonist may be warranted in some instances, but it is associated with the risk of precipitating an acute withdrawal syndrome.

10.5 General Considerations for Overdose

Management of severe Lazanda overdose includes: securing a patent airway, assisting or controlling ventilation, and establishing intravenous access. In the presence of hypoventilation or apnea, assist or control ventilation, and administer oxygen as indicated.

Carefully observe and appropriately manage overdosed patients until their clinical condition is well controlled.

Although muscle rigidity interfering with respiration has not been observed following the use of Lazanda, this is possible with fentanyl and other opioids. If it occurs, manage by the use of assisted or controlled ventilation, by administration of an opioid antagonist, and, as a final alternative, by the administration of a neuromuscular blocking agent.

11 DESCRIPTION

Lazanda (fentanyl) nasal spray is a liquid formulation of fentanyl citrate intended for intranasal transmucosal administration. The product consists of a practically clear to clear, colorless, aqueous solution of fentanyl citrate in a glass multidose container to which is attached a metered-dose nasal spray pump with a visual and audible spray counter. Each actuation is designed to deliver a spray of 100 mcL of solution containing 100 mcg or 400 mcg fentanyl base, respectively. This enables doses of 100 mcg or 400 mcg to be administered using a single spray into one nostril (1 spray) and 200 mcg or 800 mcg to be administered using a single spray into both nostrils (2 sprays).

Active ingredient: Fentanyl citrate, USP is N-(l-phenethyl-4-piperidyl) propionanilide citrate (1:1). Fentanyl is a highly lipophilic compound (octanol-water partition coefficient at pH 7.4 is 816:1). Fentanyl citrate is sparingly soluble in water (1:40). The molecular weight of the free base and citrate salt are 336.5 and 528.6, respectively. The pKa is 8.4. The compound has the following structural formula:

Lazanda is available in 2 strengths of nasal spray: 100 mcg fentanyl (yellow label) and 400 mcg fentanyl (violet label). The strength is expressed as the amount of fentanyl free base per spray, e.g., the 100 mcg strength provides 100 mcg of fentanyl free base per 100 mcL spray.

Inactive ingredients: mannitol, pectin, phenylethyl alcohol, propylparaben, sucrose, water. Sodium hydroxide and/or hydrochloric acid are added if required for pH adjustment.

12 CLINICAL PHARMACOLOGY

12.1 Mechanism of Action

Fentanyl is a pure opioid agonist whose principal therapeutic action is analgesia. Other members of the class known as opioid agonists include substances such as morphine, oxycodone, hydromorphone, codeine, and hydrocodone.

12.2 Pharmacodynamics

Pharmacological effects of opioid agonists include anxiolysis, euphoria, feelings of relaxation, respiratory depression, constipation, miosis, cough suppression, and analgesia. Like all pure opioid agonist analgesics, with increasing doses there is increasing analgesia, unlike with mixed agonist/antagonists or non-opioid analgesics, where there is a limit to the analgesic effect with increasing doses. With pure opioid agonist analgesics, there is no defined maximum dose; the ceiling to analgesic effectiveness is imposed only by side effects, the more serious of which may include somnolence, respiratory depression and death.

Analgesia: In general, the effective concentration and the concentration at which toxicity occurs increase with increasing tolerance to any and all opioids.

The rate of development of tolerance varies widely among individuals. As a result, individually titrate the dose of Lazanda to achieve the desired effect. [see Dosage and Administration (2)].

Central Nervous System: The precise mechanism of the analgesic action is unknown although fentanyl is known to be a mu-opioid receptor agonist. Specific CNS opioid receptors for endogenous compounds with opioid-like activity have been identified throughout the brain and spinal cord and play a role in the analgesic effects of this drug.

Fentanyl produces respiratory depression by direct action on brain stem respiratory centers. The respiratory depression involves a reduction in the responsiveness of the brain stem to increases in carbon dioxide and to electrical stimulation.

Fentanyl causes miosis even in total darkness. Pinpoint pupils are a sign of opioid overdose but are not pathognomonic (e.g., pontine lesions of hemorrhagic or ischemic origin may produce similar findings).

Gastrointestinal System: Fentanyl causes a reduction in motility associated with an increase in smooth muscle tone in the antrum of the stomach and in the duodenum. Digestion of food is delayed in the small intestine and propulsive contractions are decreased. Propulsive peristaltic waves in the colon are decreased, while tone may be increased to the point of spasm resulting in constipation. Other opioid-induced effects may include a reduction in gastric, biliary, and pancreatic secretions, spasm of the sphincter of Oddi, and transient elevations in serum amylase.

Cardiovascular System: Fentanyl may produce release of histamine with or without associated peripheral vasodilation. Manifestations of histamine release and/or peripheral vasodilation may include pruritus, flushing, red eyes, sweating, and/or orthostatic hypotension.

Endocrine System: Opioid agonists have been shown to have a variety of effects on the secretion of hormones. Opioids inhibit the secretion of ACTH, cortisol, and luteinizing hormone (LH) in humans. They also stimulate prolactin, growth hormone (GH) secretion, and pancreatic secretion of insulin and glucagon in humans and other species (e.g., rats and dogs). Thyroid stimulating hormone (TSH) has been shown to be both inhibited and stimulated by opioids.

Respiratory System: All opioid mu-receptor agonists, including fentanyl, produce dose-dependent respiratory depression. The risk of respiratory depression is less in patients receiving chronic opioid therapy who develop tolerance to respiratory depression and other opioid effects.

Serious or fatal respiratory depression can occur even at recommended doses. Fentanyl depresses the cough reflex as a result of its CNS activity. Although not observed with Lazanda, in clinical trials, fentanyl given rapidly by intravenous injection in large doses has interfered with respiration by causing rigidity in the muscles of respiration. Physicians and other healthcare providers should be aware of this potential complication. [see Boxed Warning - Warning: Risk of Respiratory Depression, Medication Errors, Abuse Potential, Contraindications (4), Warnings and Precautions (5), Adverse Reactions (6), and Overdosage (10) for additional information on hypoventilation].

12.3 Pharmacokinetics

Absorption: In a study that compared the relative bioavailability of Lazanda and an oral transmucosal fentanyl citrate product, the bioavailability of fentanyl from Lazanda was approximately 20% higher. Fentanyl is absorbed from the nasal mucosa following intranasal administration of Lazanda, with median Tmax values ranging from 15-21 min after administration of a single dose. Cmax and AUC values for fentanyl following administration of Lazanda increase linearly over the 100- to 800-mcg dose range.

Mean plasma concentration versus time profiles are presented in Figure 1. Mean pharmacokinetic parameters are presented in Table 3.

Figure 1.
Mean Plasma Fentanyl Concentration (pg/mL) in Normal Subjects Receiving 100, 200, 400 and 800 mcg Lazanda or 200 mcg OTFC

Table 3. Pharmacokinetic Parameters in Normal Subjects Receiving 100, 200, 400, and 800 mcg of Lazanda or 200 mcg OTFC
 | Lazanda |  |  |  | OTFC
PHARMACOKINETIC PARAMETERS | 100 mcg | 200 mcg | 400 mcg | 800 mcg | 200 mcg
Tmax, hours median (range) | 0.33 (0.08–1.50) | 0.25 (0.17–1.60) | 0.35 (0.25–0.75) | 0.34 (0.17–3.00) | 1.50 (0.50–8.00)
Cmax, pg/mL Mean (%CV) | 351.5 (51.3) | 780.8 (48.4) | 1552.1 (26.2) | 2844.0 (56.0) | 317.4 (29.9)
AUCinf, pg.hour/mL Mean (%CV) | 2460.5 (17.9) | 4359.9 (29.8) | 7513.4 (26.7) | 17272 (48.9) | 3735.0 (32.8)
t1/2, hour Mean (%CV) | 21.9 (13.6) | 24.9 (51.3) | 15.0 (24.7) | 24.9 (92.5) | 18.6 (31.4)

In a pharmacokinetic study that evaluated multiple-dose pharmacokinetics of Lazanda when two doses of Lazanda are administered in the same nostril and are separated by a 1, 2 or 4 h time lapse, Cmax2 (Cmax after second administration) was greater than Cmax1 (Cmax after first administration), by 30% when Lazanda was administered 1 h apart, by 25% when Lazanda was administered 2 h apart and by 10% when Lazanda was administered 4 h apart. Based on these results and based on Tmax range of Lazanda observed across pharmacokinetic studies, and frequency of breakthrough pain episodes in a cancer population, a waiting period of 2 h between two consecutive doses of Lazanda is recommended [see Dosage and Administration (2)].

In a pharmacokinetic study to evaluate differences in Lazanda absorption in individuals with induced allergic (seasonal) rhinitis, no clinically meaningful differences were observed in rate or extent of exposure to fentanyl, when compared to the Asymptomatic (Unchallenged) state, indicating that presence of allergic rhinitis does not affect Lazanda absorption. This study also assessed differences in Lazanda absorption, if any, when co-administered with oxymetazoline, a nasal decongestant in subjects undergoing treatment for seasonal allergic rhinitis. Mean Cmax values for Treated arm (Rhinitis treated with oxymetazoline) were about 32% and 40% lower and mean AUCt values were about 10% and 17% lower for Ragweed and Tree pollen induced cohorts respectively as compared to the Asymptomatic arm in each cohort. In addition, mean Tmax of Lazanda in the Treated arm was 0.75 h (range 0.08-3 h) for the Ragweed pollen induced cohort and 1.25 h (range 0.08-3 h) for Tree pollen induced cohort as compared to 0.25 h (0.17-1 h) and 0.33 h (0.17-2 h) for the Asymptomatic arm in each cohort respectively. These results indicate that co-administration with oxymetazoline leads to lower peak plasma concentrations and delayed Tmax of Lazanda [see Drug Interactions (7.2)].

Distribution: Fentanyl is highly lipophilic. The plasma protein binding of fentanyl is 80% to 85%. The main binding protein is alpha-1-acid glycoprotein, but both albumin and lipoproteins contribute to some extent. The mean volume of distribution at steady state (Vss) was 4 L/kg.

Metabolism: The metabolic pathways following intranasal administration of Lazanda have not been characterized in clinical studies. The progressive decline of fentanyl plasma concentrations results from the uptake of fentanyl in the tissues and biotransformation in the liver. Fentanyl is metabolized in the liver and in the intestinal mucosa to norfentanyl by cytochrome P450 3A4 isoform. In animal studies, norfentanyl was not found to be pharmacologically active.

Elimination: The disposition of fentanyl following intranasal administration of Lazanda has not been characterized in a mass balance study. Fentanyl is primarily (more than 90%) eliminated by biotransformation to N-dealkylated and hydroxylated inactive metabolites. Less than 7% of the administered dose is excreted unchanged in the urine, and only about 1% is excreted unchanged in the feces. The metabolites are mainly excreted in the urine, while fecal excretion is less important.

The total plasma clearance of fentanyl following intravenous administration is approximately 42 L/h.

13 NONCLINICAL TOXICOLOGY

13.1 Carcinogenesis, Mutagenesis, Impairment of Fertility

Long-term studies in animals have not been performed to evaluate the carcinogenic potential of fentanyl.

Fentanyl citrate was not mutagenic in the in vitro Ames reverse mutation assay in S. typhimurium or E. coli, or the mouse lymphoma mutagenesis assay, and was not clastogenic in the in vivo mouse micronucleus assay.

Fentanyl has been shown to impair fertility in rats at doses of 30 mcg/kg subcutaneously. Conversion to human equivalent doses indicates this is within the range of the human recommended dosing for Lazanda.

14 CLINICAL STUDIES

The efficacy of Lazanda was evaluated in one clinical trial in opioid tolerant adult patients experiencing breakthrough cancer pain. Breakthrough cancer pain was defined as a transient flare of moderate-to-severe pain occurring in patients experiencing persistent cancer pain otherwise controlled with maintenance doses of opioid medications including at least 60 mg of oral morphine/day or an equianalgesic dose of another opioid (which could be fentanyl) for a week or longer. All patients were on stable doses of either long-acting oral opioids or transdermal fentanyl for their persistent cancer pain.

The clinical trial included an open-label titration phase where a dose was identified that provided adequate analgesia with tolerable side effects, within the range of 100 to 800 mcg. In the double-blind, placebo-controlled portion of the study, patients who were titrated to an adequate dose were randomized to a blinded sequence of 10 treatments with 7 being the identified dose of Lazanda and 3 being placebo.

Of the patients who enrolled in the study, 73% achieved an adequate dose during the titration phase, 6% withdrew for lack of effective pain relief, and 5% withdrew due to adverse events.

The distribution of final titrated doses is shown in Table 4. The final titrated dose of Lazanda for breakthrough pain was not predicted from the daily maintenance dose of opioid used to manage the persistent cancer pain and, therefore, the dose was determined by titration starting at 100 mcg.

Table 4. Dose of Lazanda Following Initial Titration (ITT population)
Lazanda Dose | (N=83) n (%)
100 mcg | 12 (14)
200 mcg | 7 (8)
400 mcg | 27 (33)
800 mcg | 37 (45)

The primary outcome measure, the mean sum of the pain intensity difference at 30 minutes (SPID30), was statistically significantly higher for Lazanda than for placebo (see Figure 2).

Figure 2. Pain Intensity Differences (PID) following Lazanda or Placebo in Adult Patients with Breakthrough Cancer Pain

16 HOW SUPPLIED/STORAGE AND HANDLING

16.1 Storage and Handling of Lazanda

Lazanda is supplied in glass bottles, containing 8 sprays of 100 mcL containing 100 mcg/100 mcL or 400 mcg/100 mcL concentration solution. Each bottle is supplied in a child-resistant container.

The amount of fentanyl contained in Lazanda can be fatal to a child, individual for whom it is not prescribed or non-opioid tolerant adult. Patients and their caregivers must be instructed to keep Lazanda out of the reach of children [see Boxed Warning - Warning: Risk of Respiratory Depression, Medication Errors, Abuse Potential, Warnings and Precautions (5), and Patient Counseling Information (17.1)].

Store at up to 25°C. Do not freeze.

Return the bottle to the child-resistant container after each use. Put the bottle in its child-resistant container and the pouch in the cardboard carton and store securely out of the reach of children and protect from light.

Note: Carton and bottle label colors are a secondary aid in product identification. Confirm the printed dosage before dispensing.

16.2 Disposal of Lazanda

Patients and caregivers must be instructed to properly dispose of all unused, partially used and used Lazanda bottles. The remaining liquid in all bottles must be sprayed into the pouch, provided in the pack, for safe disposal as soon as possible.

The patient should be instructed how to do this correctly. If there are any unwanted therapeutic sprays remaining in the bottle, instruct the patient to spray these into the pouch until the number "8" appears in the counting window and there are no more full therapeutic sprays obtainable from the bottle. After the counter has advanced to "8", the patient should continue to push down on the finger grips a total of four times in order to expel any residual medicine from the bottle. After the 8 therapeutic sprays have been emitted, the patient will not hear a click and the counter will not advance beyond "8"; further sprays emitted will not be full sprays and should always be trapped in the pouch, not used therapeutically.

The patient and caregiver must be instructed to seal the pouch and place both it and the empty bottle into the child-resistant storage container. Hands must be washed with soap and water immediately after handling the pouch. The patient must discard the child-resistant container containing the pouch and the bottle in the trash.

The patient or caregiver must continue to store the Lazanda bottle in the specially provided child-resistant container and the pouch out of the reach of children until proper disposal, as described above, is possible.

Instruct the patient to dispose of the Lazanda bottle and start a new one if:

- it has been 5 days or more since they last used the bottle of Lazanda
- it has been 14 days or more since they primed the bottle.

In the event that caregivers or patients require additional assistance with the disposal of Lazanda bottles, call the Archimedes Pharma toll-free number (1-866-435-6775).

16.3 How Supplied

Lazanda is supplied in a 5.3 ml capacity clear glass bottle with an attached metered-dose nasal spray pump incorporating a visual and audible spray counter, and a protective dust cover. Each bottle contains a net fill weight of 1.57 grams and, after priming, delivers 8 sprays. The pump will remain primed for up to 5 days after priming or use. The nasal spray delivers 8 full sprays. There are 2 product strengths and each 100 mcL spray contains either 100 mcg or 400 mcg of fentanyl. Each bottle is supplied in a child-resistant container.

Bottles in their child-resistant containers are supplied in cartons containing 1 or 4 bottles with instructions for use.

Each carton contains one carbon-lined pouch per bottle for disposal of priming sprays, unwanted doses and residual fentanyl solution.

Lazanda Dosage Strength (fentanyl base) | Number of Bottles per Carton | NDC Number
100 mcg | 1 | 51772-311-01
100 mcg | 4 | 51772-311-04
400 mcg | 1 | 51772-314-01
400 mcg | 4 | 51772-314-04

17 PATIENT COUNSELING INFORMATION

See FDA-approved patient labeling (Medication Guide)

17.1 Patient/Caregiver Instructions

- Before initiating treatment with Lazanda, explain the statements below to patients and/or caregivers. Instruct patients to read the Medication Guide each time Lazanda is dispensed because new information may be available.
- TIRF REMS Access Program
  - Outpatients must be enrolled in the TIRF REMS Access program before they can receive Lazanda.
  - Allow patients the opportunity to ask questions and discuss any concerns regarding Lazanda or the TIRF REMS Access program.
  - As a component of the TIRF REMS Access program, prescribers must review the contents of the Lazanda Medication Guide with every patient before initiating treatment with Lazanda.
  - Advise the patient that Lazanda is available only from pharmacies that are enrolled in the TIRF REMS Access program, and provide them with the telephone number and website for information on how to obtain the drug.
  - Advise the patient that only enrolled health care providers may prescribe Lazanda.
  - Patient must sign the Patient-Prescriber Agreement to acknowledge that they understand the risks of Lazanda.
  - Advise patients that they may be requested to participate in a survey to evaluate the effectiveness of the TIRF REMS Access program.
- Instruct patients and their caregivers that the amount of fentanyl contained in a bottle can be fatal to a child. Patients and their caregivers must be instructed to keep Lazanda in its child-resistant container at all times and to store it and the pouch securely and out of the reach of children.
- Instruct patients how to safely dispose of the priming sprays and any remaining fentanyl solution in the pouch provided before disposing of both the empty bottle and the pouch inside the child-resistant container in the trash.
- Instruct patients not to take Lazanda for acute pain, postoperative pain, pain from injuries, headache, migraine, or any other short-term pain, even if they have taken other opioid analgesics for these conditions.
- Instruct patients on the meaning of opioid tolerance and Lazanda is only to be used as a supplemental pain medication for patients with pain requiring regular opioids, who have developed tolerance to the opioid medication and who need additional opioid treatment of breakthrough pain episodes.
- Instruct patients that if they are not taking an opioid medication on a regular around-the-clock basis, they must not take Lazanda.
- Instruct patients that they MUST wait at least 2 hours before treating another episode of breakthrough pain with Lazanda.
- Instruct patients NOT to share Lazanda and that sharing Lazanda with anyone else could result in the other individual's death due to overdose.
- Advise patients that Lazanda contains fentanyl, which is a pain medication similar to hydromorphone, methadone, morphine, oxycodone, and oxymorphone.
- Advise patients that the active ingredient in Lazanda, fentanyl, is a drug that some people abuse. Lazanda is to be taken only by the patient for whom it was prescribed, and protected from theft or misuse in the work or home environments.
- Instruct patients to talk to their doctor if breakthrough pain is not alleviated or worsens after taking Lazanda.
- Instruct patients to use Lazanda exactly as prescribed by their doctor and not to take Lazanda more often than prescribed.
- Caution patients that Lazanda can affect a person's ability to perform activities that require a high level of attention (such as driving or using heavy machinery). Warn patients taking Lazanda of these dangers and counsel accordingly.
- Warn patients not to combine Lazanda with alcohol, sleep aids, or tranquilizers except by order of the prescribing physician, because dangerous additive effects may occur resulting in serious injury or death.
- Inform female patients that if they become pregnant or plan to become pregnant during treatment with Lazanda to ask their doctor about the effects that Lazanda (or any medicine) may have on them and their unborn child.
- Instruct the patient to dispose of the Lazanda bottle and start a new one if:
  - it has been 5 days or more since they last used the bottle of Lazanda
  - it has been 14 days or more since they primed the bottle.
- Physicians and dispensing pharmacists must specifically question patients or caregivers about the presence of children in the home (on a full time or visiting basis) and counsel them regarding the dangers to children from inadvertent exposure.

17.2 Disposal of Used Lazanda Bottles

- Instruct patients and caregivers to properly dispose of all unused, partially used and used Lazanda bottles as soon as no longer needed.
- Instruct patients that, to dispose of Lazanda properly, the remaining liquid in all bottles must be sprayed into the pouch provided in the pack for safe disposal as soon as possible. This includes any unwanted therapeutic sprays remaining in the bottle. After the counter has advanced to "8", the patient should continue to push down on the finger grips a total of four times in order to expel any residual medicine from the bottle. After the 8 therapeutic sprays have been emitted, the patient will not hear a click and the counter will not advance beyond "8"; further sprays emitted will not be full sprays and should always be trapped in the pouch, not used therapeutically.
- Instruct the patient and caregiver to seal the pouch and to place both the empty bottle and the sealed pouch into the child-resistant storage container and discard in the trash. Lazanda must be stored in the specially provided child-resistant container out of the reach of children until proper disposal is possible.
- Instruct the patient and caregiver to wash their hands with soap and water immediately after handling the pouch.
- If the pouch is lost, instruct the patient and caregiver to use a pouch from another Lazanda pack to prime and dispose of unused medicine from the current bottle as well as from the next bottle. If they do not have an empty pouch available, the patient or caregiver can order one by calling 1-866-435-6775. They will receive the replacement pouch in the mail.

Rx Only.

Distributed by Archimedes Pharma US Inc.
One Crossroads Drive
Bedminster NJ 07921

For information about this product call:
1- 866-435-6775

U.S. Patent Nos. 6,432,440 and 8,216,604
Lazanda is a registered trademark of Archimedes Development Ltd.
© 2012 Archimedes Development Ltd.

PIUS-300-4 ; PPIUS-300-4

Medication Guide

Lazanda® (La-ZAN-da) CII

(fentanyl)
nasal spray
100 mcg, 400 mcg

BOXED WARNING

IMPORTANT:

Do not use Lazanda unless you are regularly using another opioid pain medicine around-the-clock for your cancer pain and your body is used to these medicines (this means that you are opioid tolerant). You can ask your healthcare provider if you are opioid tolerant.

Keep Lazanda in a safe place away from children.

Get emergency medical help right away if:

- a child takes Lazanda. Lazanda can cause an overdose and death in any child who takes it
- an adult who has not been prescribed Lazanda takes it
- an adult who is not already taking opioids around-the-clock takes Lazanda

These are medical emergencies that can cause death.

Read this Medication Guide completely before you start taking Lazanda and each time you get a new prescription. There may be new information. This Medication Guide does not take the place of talking to your healthcare provider about your medical condition or your treatment. Be sure to share this important information with members of your household and other caregivers.

What is the most important information I should know about Lazanda?

Lazanda can cause life-threatening breathing problems that can lead to death:

1. Do not take Lazanda if you are not opioid tolerant.
2. If you stop taking your around-the-clock opioid pain medicine for your cancer, you must stop taking Lazanda. You may no longer be opioid tolerant. Talk to your healthcare provider about how to treat your pain.
3. Take Lazanda exactly as prescribed by your healthcare provider.
  - You must not take more than 1 dose of Lazanda for each episode of breakthrough cancer pain.
  - You must wait two hours before treating a new episode of breakthrough cancer pain with Lazanda. See the Medication Guide section "How should I use Lazanda?" and the "Instructions for Use" section at the end of this Medication Guide for detailed information about how to use Lazanda the right way.
4. Do not switch from Lazanda to other medicines that contain fentanyl without talking with your healthcare provider. The amount of fentanyl in a dose of Lazanda is not the same as the amount of fentanyl in other medicines that contain fentanyl. Your healthcare provider will prescribe a starting dose of Lazanda that may be different than other fentanyl-containing medicine you may have been taking.
5. Do not take Lazanda for short-term pain that you would expect to go away in a few days, such as:
  - pain after surgery
  - headache or migraine
  - dental pain
6. Never give Lazanda to anyone else, even if they have the same symptoms you have. It may harm them or even cause death.

Lazanda is a federally controlled substance (CII) because it is a strong opioid (narcotic) pain medicine that can be misused by people who abuse prescription medicines or street drugs.

- Prevent theft, misuse or abuse. Keep Lazanda in a safe place to protect it from being stolen. Lazanda can be a target for people who abuse opioid (narcotic) medicines or street drugs.
- Selling or giving away this medicine is against the law.

Lazanda is available only through a program called the TIRF REMS ACCESS program. To receive Lazanda, you must:

- talk to your healthcare provider
- understand the benefits and risks of Lazanda
- agree to all of the instructions
- sign the Patient-Prescriber Agreement form

What is Lazanda®?

- Lazanda is a prescription medicine that contains the medicine fentanyl.
- Lazanda is used to manage breakthrough pain in adults with cancer (18 years of age and older) who are already routinely taking other opioid pain medicines around-the-clock for cancer pain.
- Lazanda is started only after you have been taking other opioid pain medicines and your body has become used to them (you are opioid tolerant). Do not use Lazanda if you are not opioid tolerant.
- You must stay under your healthcare provider's care while taking Lazanda.
- Lazanda is a nasal spray. You use Lazanda by placing the nozzle attached to the bottle in your nostril and spraying. See the Medication Guide section "How should I use Lazanda?"
- Lazanda is only:
  - available through the TIRF REMS ACCESS program
  - given to people who are opioid tolerant

It is not known if Lazanda is safe and effective in children under 18 years of age.

Who should not take Lazanda?

Do not take Lazanda:

- if you are not opioid tolerant. Opioid tolerant means that you are already taking other opioid (narcotic) pain medicines around-the-clock for your cancer pain and your body is used to these medicines
- for short-term pain that you would expect to go away in a few days, such as:
  - pain after surgery
  - headache or migraine
  - dental pain
- if you are allergic to fentanyl or any of the ingredients in Lazanda. See the end of this Medication Guide for a complete list of other ingredients in Lazanda.

What should I tell my healthcare provider before taking Lazanda?

Before taking Lazanda, tell your healthcare provider if you:

- have trouble breathing or lung problems such as asthma, wheezing, or shortness of breath
- have or had a head injury or brain problem
- have liver or kidney problems
- have seizures
- have a slow heart rate or other heart problems
- have low blood pressure
- have mental health problems including major depression, schizophrenia, or hallucinations (seeing or hearing things that are not there)
- have a past or present drinking problem (alcoholism), or a family history of drinking problems
- have a past or present drug abuse problem or addiction problem, or a family history of a drug abuse problem or addiction problem
- have any other medical conditions
- are pregnant or planning to become pregnant. Lazanda may cause serious harm to your unborn baby
- are breastfeeding or plan to breastfeed. Lazanda can pass into your breast milk. It can cause serious harm to your baby. Do not use Lazanda while breastfeeding

Tell your healthcare provider about all the medicines you take, including prescription and nonprescription medicines, vitamins, and herbal supplements. Some medicines may cause serious or life-threatening medical problems when taken with Lazanda. Sometimes, the doses of certain medicines and Lazanda need to be changed if used together.

- Do not take any medicine while using Lazanda until you have talked to your healthcare provider. Your healthcare provider will tell you if it is safe to take other medicines while you are using Lazanda.
- Be very careful about taking other medicines that may make you sleepy, such as other pain medicines, anti-depressants, sleeping pills, anti-anxiety medicines, anti-histamines, or tranquilizers.

Know the medicines you take. Keep a list of them to show your healthcare provider and pharmacist when you get a new medicine.

How should I use Lazanda?

Before you can begin to use Lazanda:

- Your healthcare provider will explain the TIRF REMS ACCESS program to you.
- You will sign the TIRF REMS ACCESS program Patient-Prescriber Agreement form.
- Lazanda is only available at pharmacies that are part of the TIRF REMS ACCESS program. Your healthcare provider will let you know the pharmacy closest to your home where you can have your Lazanda prescription filled.

Using Lazanda:

- Use Lazanda exactly as your healthcare provider tells you to. Do not use Lazanda more often than prescribed.
- See the "Instructions for Use" section at the end of this Medication Guide for detailed information about the right way to use and throw away (dispose of) Lazanda.
- Lazanda comes in 2 strengths. When you are first prescribed Lazanda, your healthcare provider will start you with the lower strength medicine, and will change the dose until you and your healthcare provider find the right dose for you. Do not change your dose of Lazanda unless your healthcare provider tells you to.
- The beginning dose of Lazanda is always 1 spray in one of your nostrils.
- Always use 1 dose of Lazanda for an episode of breakthrough cancer pain exactly as your healthcare provider tells you to. As your dose is adjusted, your healthcare provider will tell you whether your dose of Lazanda is 1 or 2 sprays:
  - 1 spray is given by spraying 1 time into one of your nostrils
  - 2 sprays are given by spraying 1 time into each nostril for a total of 2 sprays.
    You must never use more than 2 sprays (1 spray in each nostril) for an episode of breakthrough pain.
- If an episode of breakthrough cancer pain continues for more than 30 minutes after you take a dose of Lazanda, follow your healthcare provider's instructions about taking a short-acting opioid pain medicine to manage your pain.
- Wait at least 2 hours before treating a new episode of breakthrough cancer pain with Lazanda.
- It is important for you to keep taking your around-the-clock opioid pain medicine while using Lazanda.
- Talk to your healthcare provider if your dose of Lazanda does not relieve your breakthrough cancer pain. Your healthcare provider will decide if your dose of Lazanda needs to be changed.
- Talk to your healthcare provider if you have more than 4 episodes of breakthrough cancer pain per day. The dose of your around-the-clock opioid pain medicine may need to be adjusted.
- The Lazanda nasal spray pump provides a total of 8 full sprays. When there is a red number "8" in the counting window, you have used all the medicine in the bottle. You may still see medicine in the bottle, but there is not enough for a full dose. Do not try to take more than 8 sprays from a bottle of Lazanda.
- If you use too much Lazanda or overdose, you or your caregiver should call for emergency medical help or have someone take you to the nearest hospital emergency room right away.

What should I avoid while using Lazanda?

- Do not drive, operate heavy machinery, or do other dangerous activities until you know how Lazanda affects you. Lazanda can make you sleepy. Ask your healthcare provider when it is okay to do these activities.
- Do not drink alcohol while using Lazanda. It can increase your chance of getting dangerous side effects.
- Avoid drinking grapefruit juice during treatment with Lazanda.

What are the possible side effects of Lazanda?

1. Breathing problems that can become life-threatening. See "What is the most important information I should know about Lazanda?"
  - Call your healthcare provider or get emergency medical help right away if you:
    - have trouble breathing
    - have drowsiness with slowed breathing
    - have shallow breathing (little chest movement with breathing)
    - feel faint, very dizzy, confused, or have other unusual symptoms

  These symptoms can be a sign that you have taken too much Lazanda or the dose is too high for you. These symptoms may lead to serious problems or death if not treated right away. If you have any of these symptoms, do not take any more Lazanda until you have talked to your healthcare provider.

2. Decreased blood pressure. This can make you feel dizzy or lightheaded if you get up too fast from sitting or lying down.
3. Physical dependence. Do not stop taking Lazanda or any other opioid without talking to your healthcare provider. You could become sick with uncomfortable withdrawal symptoms because your body has become used to these medicines. Physical dependency is not the same as drug addiction.
4. A chance of abuse or addiction. The chance is higher if you are or have ever been addicted to or abused other medicines, street drugs, or alcohol, or if you have a history of mental problems.

The most common side effects of Lazanda are:

- vomiting
- nausea
- constipation
- dizziness
- fever

Constipation (not often enough or hard bowel movements) is a very common side effect of pain medicines (opioids) including Lazanda and is unlikely to go away without treatment. Talk to your healthcare provider about dietary changes and the use of laxatives (medicines to treat constipation) and stool softeners to prevent or treat constipation while taking Lazanda.

Tell your healthcare provider if you have any side effect that bothers you or that does not go away.

These are not all the possible side effects of Lazanda. For more information, ask your healthcare provider or pharmacist.

Call your doctor for medical advice about side effects. You may report side effects to FDA at 1-800-FDA-1088.

How should I store Lazanda?

- Always keep Lazanda in a safe place away from children and from anyone for whom it has not been prescribed. Protect Lazanda from theft.
- Store Lazanda at up to 77°F (25°C). Do not freeze Lazanda.
- Lazanda comes in a clear glass bottle with an attached nasal spray pump and a protective cap.
- Store Lazanda in the child-resistant container that comes with it at all times except when you are using it. Store the Lazanda child-resistant container and pouch in the cardboard box when not in use.
- Keep Lazanda away from light.
- See the "Instructions for Use" section at the end of this Medication Guide for information about the right way to dispose of Lazanda when no longer needed.

General information about Lazanda

Medicines are sometimes prescribed for purposes other than those listed in a Medication Guide. Use Lazanda only for the purpose for which it was prescribed. Do not give Lazanda to other people, even if they have the same symptoms you have. Lazanda can harm other people and even cause death. Sharing Lazanda is against the law.

This Medication Guide summarizes the most important information about Lazanda. If you would like more information, talk with your healthcare provider. You can ask your pharmacist or healthcare provider for information about Lazanda that is written for healthcare professionals.

For more information about the TIRF REMS ACCESS program, go to www.tirfremsaccess.com or call 1-866-822-1483.

What are the ingredients in Lazanda?

Active ingredient: fentanyl citrate
Inactive ingredients: mannitol, pectin, phenylethyl alcohol, propylparaben, sucrose, water

Instructions for Use

Before you take Lazanda it is important that you read, understand, and follow the full Medication Guide, including these Instructions for Use. Ask your healthcare provider or pharmacist if you have any questions about the right way to prepare, use, or dispose of Lazanda. Wash your hands with soap and water before and after you use Lazanda.

What will I find in the Lazanda pack?
Each Lazanda pack contains a cardboard box that includes (See Figure A):

- a Medication Guide (not shown)
- a disposal pouch (See Figure B)
- a child-resistant container, which holds 1 bottle of Lazanda.

Take the pouch and the Lazanda bottle in its child-resistant container out of the cardboard box when you are ready to use it. Keep the cardboard box and child-resistant container for storing your Lazanda. You will need to keep the pouch to safely dispose of any medicine left in the bottle. Do not remove the plastic strip from the pouch until you are ready to seal it.

- Store the Lazanda bottle in the child-resistant container whenever it is not in use.

See the section "How should I store Lazanda?" for more information about storing Lazanda.

Preparing Lazanda for use
Before you use a new bottle of Lazanda for the first time, you will need to prime (prepare) the bottle. To prime the bottle:

1. Remove the cap from the child-resistant container. To do this, squeeze the raised tabs on the cap and twist the cap to remove (See Figure C). Take the bottle of Lazanda out of the child-resistant container.
2. Remove the protective cap from the nozzle (tip) (See Figure D).
3. Place the tip of the Lazanda bottle into the opening of the pouch. Hold the Lazanda bottle upright so that the spray goes into the pouch (See Figure E).

4. Look at the counting window. A new unused bottle of Lazanda will show 2 thin red lines in the counting window in the white plastic top on the bottle (See Figure F).

  - Firmly press on the grips and then release. You will hear a "click" and you will see 1 wide red bar in the counting window (See Figure G).
  - Keep pressing and releasing the grips 3 more times (for a total of 4 times). Each time, the red bar will become smaller until you see a green bar in the counting window (See Figures H, I, J).

5. When you see the green bar, this means that Lazanda is ready for use (See Figure K).
6. Remove the tip of the bottle from the pouch.
  Do not seal the pouch. Do not throw the pouch away.
7. If you are not going to take your medicine right away
  - Replace the protective cap
  - Put the bottle in its child-resistant container. Put the child-resistant container and pouch in the cardboard box.
  - Store the box securely out of the reach of children and pets
8. Wash your hands with soap and water.

Using Lazanda

1. Check to be sure that the Lazanda bottle is ready for use. If the bottle is ready for use, you will see either a green bar (See Figure L) or a number (See Figure M) in the counting window.
2. If you have a runny nose, blow your nose now.
3. Remove the protective cap from the nozzle (tip).
4. Sit up with your head upright and hold the Lazanda bottle with your thumb on the bottom of the bottle and your first and middle fingers on the finger grips (See Figure N). Insert the tip a short distance (about ½ inch) into your nose, and point the tip toward the bridge of your nose. This will tilt the bottle slightly (See Figure O).

5. Close off the other nostril with 1 finger (See Figure P).
6. Firmly press down on the finger grips until you hear a "click".
7. Breathe in gently through your nose and out through your mouth 1 time after spraying. Do not sniff after spraying the medicine into your nose.
  - You may not feel the spray go into your nose. This is normal.
  - After you hear the click, you will see that the number in the counting window has increased by 1. This tells you that a spray has been given.
8. If your healthcare provider has prescribed a second spray, repeat steps 4 through 7, but use the other nostril.
9. After each spray, the number in the counting window will increase by 1. When you see a red number "8" in the counting window, the bottle is finished and you will no longer be able to get a full dose from it. You may still see medicine in the bottle, but there is not enough for a full dose. Do not try to take another dose of Lazanda from this bottle.

10. Stay sitting down for at least 1 minute after using Lazanda.
11. Avoid blowing your nose for at least 30 minutes after each spray.
12. Replace the protective cap on the tip of the bottle (See Figure Q). Return the bottle to the child-resistant container after each use, and store securely out of the reach of children.

Disposing of Lazanda
Dispose of the Lazanda bottle when no longer needed:

- If you have used 8 sprays from a bottle, or
- If it has been 5 days since you last used the bottle, or
- If it has been 14 days since you primed (prepared) your bottle

Before you throw away the Lazanda bottle, you must empty all the remaining medicine into the pouch. This is to protect others, especially children, from harm.

Disposal of any unused Lazanda
If you can see a number, other than 8 in the counting window, you have NOT used all 8 sprays in the bottle. There are still doses of Lazanda in the bottle.

- You must empty the remaining doses of Lazanda from the bottle
- Put tip in pouch and press and release the grips (See Figure R) until the red number "8" appears in the counting window (See Figure S).

When you see the number "8" in the counting window (See Figure S), there is still medicine in the bottle that you must spray in the pouch.

- Put the tip into the pouch.(See Figure R)
- Press and release the grips a total of 4 times (See Figure R)
  - You will feel some increased resistance when you press down
  - You will not hear a click when you press down
  - The counter will stay on the red number "8" (See Figure S)

Disposal of Bottle and Pouch

1. Put the protective cap back on the spray bottle. Put the empty bottle back into the child-resistant container.
2. Seal the pouch by removing the plastic strip from the flap and folding the flap over (See Figures T and U). Put the sealed pouch into the child–resistant container with the empty bottle.
3. Place the cap back onto the child-resistant container and twist to close.
4. Throw the child-resistant container with the empty bottle and sealed pouch inside it into the trash.
5. Wash your hands with soap and water.

If you need help with disposal of unused Lazanda bottles, call Archimedes Pharma at 1-866-435-6775 or call your local Drug Enforcement Administration (DEA) office.

If you lose the pouch, use a pouch from another Lazanda pack to prime and dispose of unused medicine from this bottle as well as from the next bottle. If you do not have an empty pouch available, you can order one by calling 1-866-435-6775. You will receive the replacement pouch in the mail.

If you need to continue using Lazanda, open a new bottle and see the Instructions for Use section of this Medication Guide about "Preparing Lazanda for Use."

This Medication Guide has been approved by the US Food and Drug Administration.

Archimedes Pharma US Inc. • One Crossroads Drive • Bedminster NJ 07921
Revised: 12/2011

Lazanda® is a registered trademark of Archimedes Development Ltd.
©2011 Archimedes Development Ltd.
All rights reserved.

MGUS300

PACKAGE LABEL

PRINCIPAL DISPLAY PANEL - 100 mcg Carton

NDC 51772-311-04

100 mcg per spray

Lazanda™
fentanyl nasal spray CII

For nasal administration only

Dispense the enclosed Medication Guide to each patient

4 bottles, containing 8 sprays each, and 4 disposal pouches

WARNING:
Keep out of the reach of children

PATIENTS MUST BE TOLERANT TO
AROUND-THE-CLOCK OPIOID THERAPY

DO NOT SUBSTITUTE LAZANDA
FOR OTHER FENTANYL PRODUCTS

Lazanda can be harmful or fatal if
given to someone for whom it was
not prescribed

Store the bottle in the child resistant
container at all times, even when finished.

PACKAGE LABEL

PRINCIPAL DISPLAY PANEL - 400 mcg Carton

NDC 51772-314-04

400 mcg per spray

Lazanda™
fentanyl nasal spray CII

For nasal administration only

Dispense the enclosed Medication Guide to each patient

4 bottles, containing 8 sprays each, and 4 disposal pouches

WARNING:
Keep out of the reach of children

PATIENTS MUST BE TOLERANT TO
AROUND-THE-CLOCK OPIOID THERAPY

DO NOT SUBSTITUTE LAZANDA
FOR OTHER FENTANYL PRODUCTS

Lazanda can be harmful or fatal if
given to someone for whom it was
not prescribed

Store the bottle in the child resistant
container at all times, even when finished.